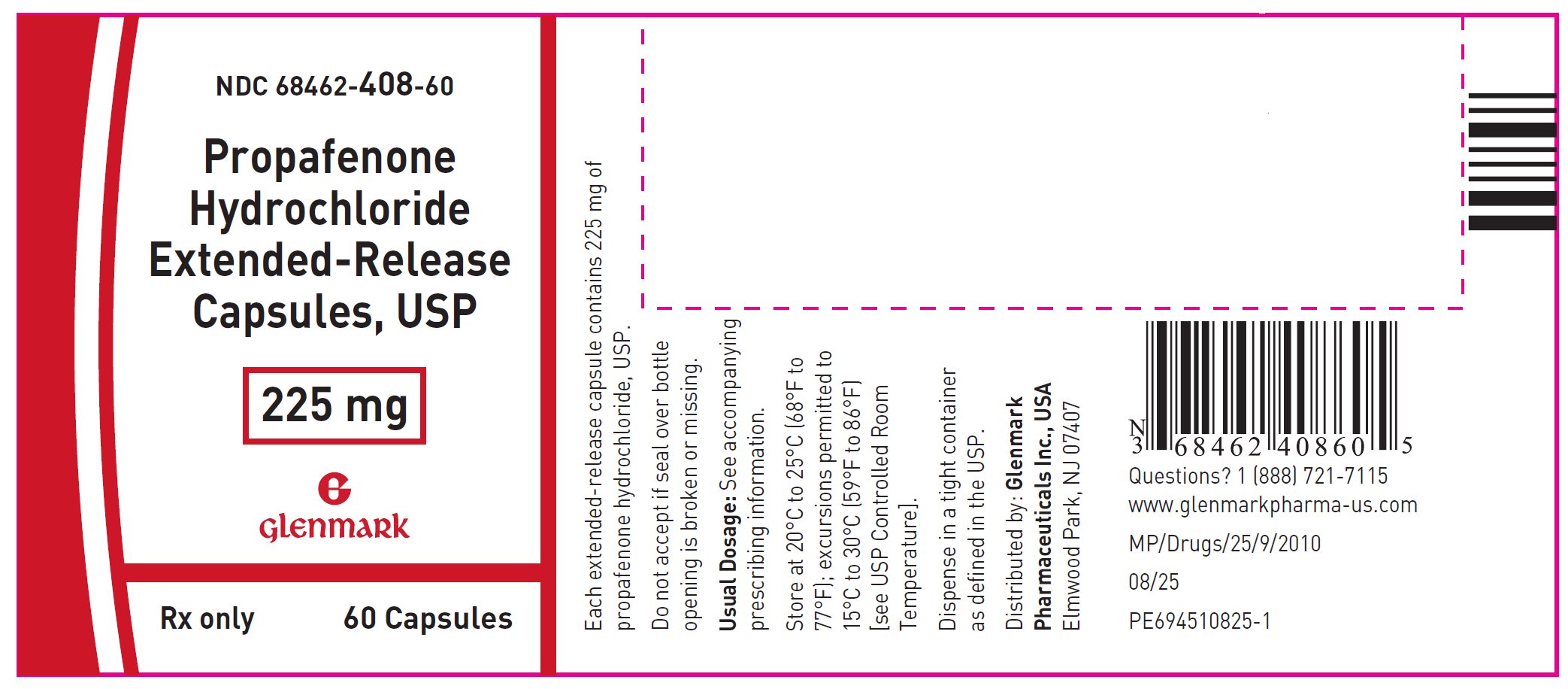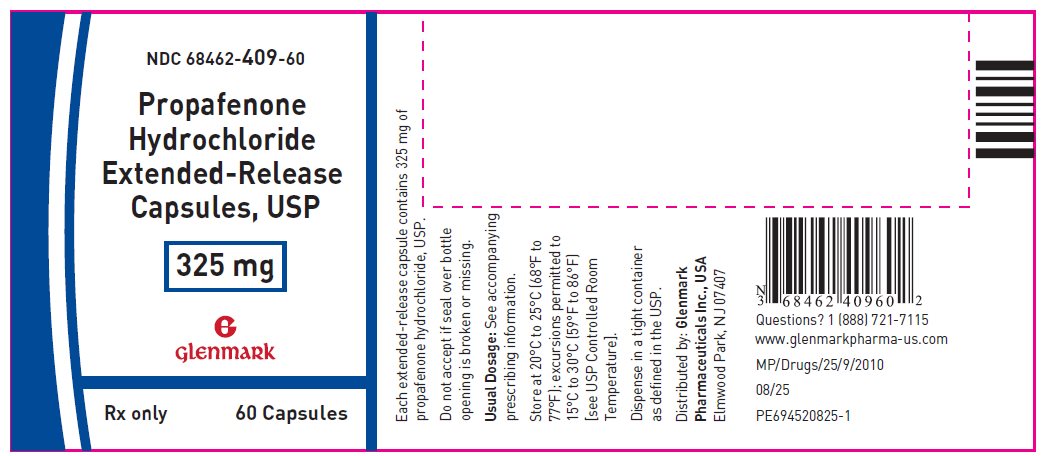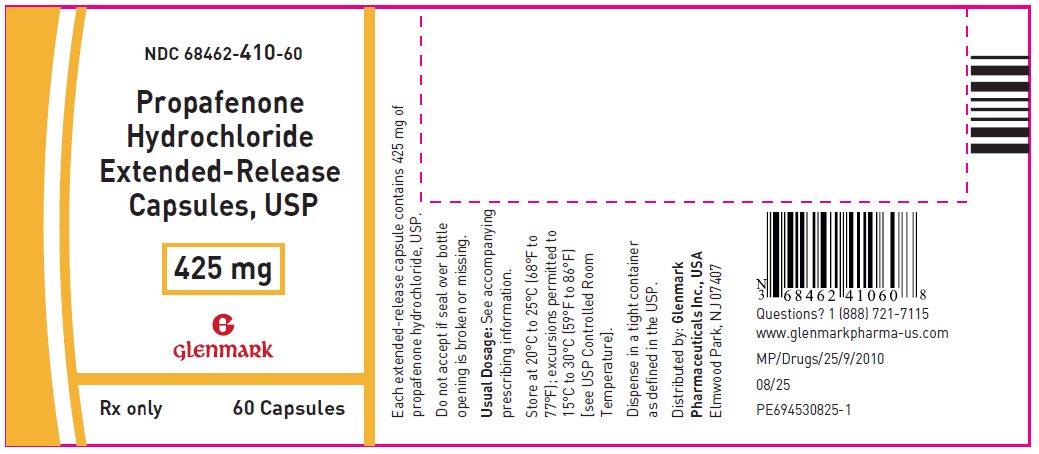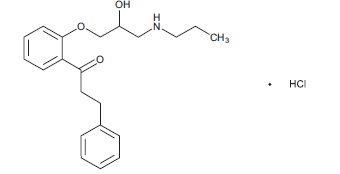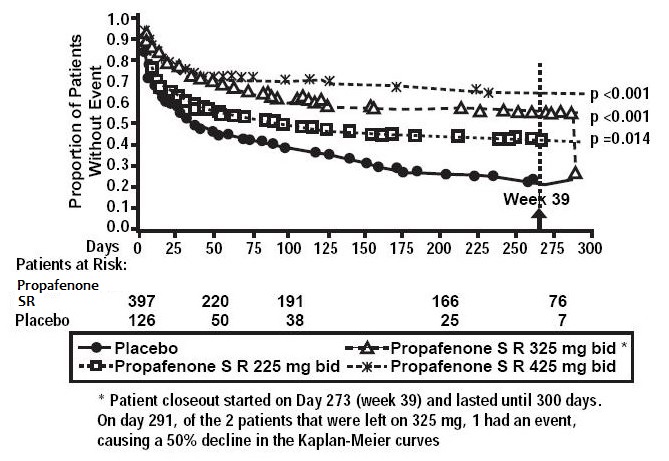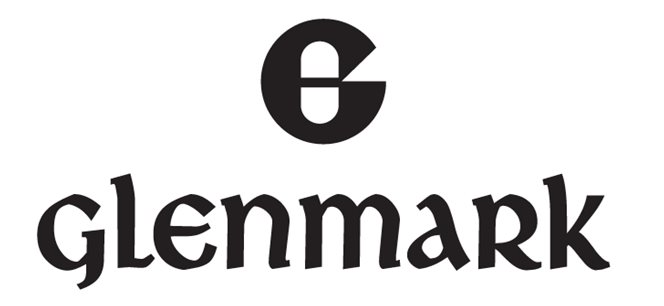 DRUG LABEL: propafenone hydrochloride
NDC: 68462-408 | Form: CAPSULE, EXTENDED RELEASE
Manufacturer: Glenmark Pharmaceuticals Inc., USA
Category: prescription | Type: HUMAN PRESCRIPTION DRUG LABEL
Date: 20260129

ACTIVE INGREDIENTS: PROPAFENONE HYDROCHLORIDE 225 mg/1 1
INACTIVE INGREDIENTS: FERROSOFERRIC OXIDE; GELATIN, UNSPECIFIED; HYPROMELLOSE, UNSPECIFIED; LACTOSE MONOHYDRATE; MAGNESIUM STEARATE; MICROCRYSTALLINE CELLULOSE; POTASSIUM HYDROXIDE; SHELLAC; SODIUM LAURYL SULFATE; TITANIUM DIOXIDE

HIGHLIGHTS OF PRESCRIBING INFORMATION

These highlights do not include all the information needed to use PROPAFENONE HYDROCHLORIDE EXTENDED-RELEASE CAPSULES safely and effectively. See full prescribing information for PROPAFENONE HYDROCHLORIDE EXTENDED-RELEASE CAPSULES.
PROPAFENONE HYDROCHLORIDE extended-release capsules, for oral use
Initial U.S. Approval: 1989

WARNING: MORTALITY

See full prescribing information for complete boxed warning.

- An increased rate of death or reversed cardiac arrest rate was seen in patients treated with encainide or flecainide (Class IC antiarrhythmics) compared with that seen in patients assigned to placebo. At present, it is prudent to consider any IC antiarrhythmic to have a significant risk of provoking proarrhythmic events in patients with structural heart disease.
- Given the lack of any evidence that these drugs improve survival, antiarrhythmic agents should generally be avoided in patients with non-life-threatening ventricular arrhythmias, even if the patients are experiencing unpleasant, but not life-threatening, symptoms or signs.

1 INDICATIONS AND USAGE

Propafenone hydrochloride extended-release capsules are an antiarrhythmic indicated to prolong the time to recurrence of symptomatic atrial fibrillation (AF) in patients with episodic (most likely paroxysmal or persistent) AF who do not have structural heart disease. (1)

Usage Considerations:

- Use in patients with permanent atrial fibrillation or with atrial flutter or paroxysmal supraventricular tachycardia (PSVT) has not been evaluated. Do not use to control ventricular rate during atrial fibrillation. (1)
- In patients with atrial fibrillation and atrial flutter, use propafenone hydrochloride extended-release capsules with drugs that increase the atrioventricular nodal refractory period. (1)
- The effect of propafenone on mortality has not been determined. (1)

2 DOSAGE AND ADMINISTRATION

- Initiate therapy with 225 mg given every 12 hours. (2)
- Dosage may be increased at a minimum of 5-day intervals to 325 mg every 12 hours and, if necessary, to 425 mg every 12 hours. (2)
- Consider reducing the dose in patients with hepatic impairment, significant widening of the QRS complex, or second- or third-degree AV block. (2)

3 DOSAGE FORMS AND STRENGTHS

Capsules: 225 mg, 325 mg, 425 mg. (3)

4 CONTRAINDICATIONS

- Heart failure (4)
- Cardiogenic shock (4)
- Sinoatrial, atrioventricular, and intraventricular disorders of impulse generation and/or conduction in the absence of pacemaker (4)
- Known Brugada Syndrome (4)
- Bradycardia (4)
- Marked hypotension (4)
- Bronchospastic disorders and severe obstructive pulmonary disease (4)
- Marked electrolyte imbalance (4)

5 WARNINGS AND PRECAUTIONS

- May cause new or worsened arrhythmias. Evaluate patients via ECG prior to and during therapy. (5.1)
- Propafenone hydrochloride extended-release capsules may unmask Brugada or Brugada-like Syndrome. Evaluate patients via ECG after initiation of therapy. (4, 5.2)
- Avoid use with other antiarrhythmic agents or drugs that prolong the QT interval. (5.3)
- Avoid simultaneous use of propafenone with both a cytochrome P450 2D6 (CYP2D6) inhibitor and a 3A4 inhibitor (CYP3A4). (5.4)
- May provoke overt heart failure. (5.5)
- May cause dose-related first-degree AV block or other conduction disturbances. Should not be given to patients with conduction defects in absence of a pacemaker. (5.6)
- May affect artificial pacemakers. Pacemakers should be monitored during therapy. (5.7)
- Agranulocytosis: Patients should report signs of infection. (5.8)
- Administer cautiously to patients with impaired hepatic and renal function. (5.9, 5.10)
- Exacerbation of myasthenia gravis has been reported. (5.11)

6 ADVERSE REACTIONS

The most commonly reported adverse events with propafenone (greater than 5% and greater than placebo) excluding those not reasonably associated with the use of the drug included the following: dizziness, palpitations, chest pain, dyspnea, taste disturbance, nausea, fatigue, anxiety, constipation, upper respiratory tract infection, edema, and influenza. (6.1)

To report SUSPECTED ADVERSE REACTIONS, contact Glenmark Pharmaceuticals Inc., USA at 1 (888) 721-7115 or FDA at 1-800-FDA-1088 or www.fda.gov/medwatch.

7 DRUG INTERACTIONS

- Inhibitors of CYP2D6, 1A2, and 3A4 may increase propafenone levels which may lead to cardiac arrhythmias. Simultaneous use with both a CYP3A4 and CYP2D6 inhibitor (or in patients with CYP2D6 deficiency) should be avoided. (7.1)
- Propafenone may increase digoxin or warfarin levels. (7.2, 7.3)
- Orlistat may reduce propafenone concentrations. Abrupt cessation of orlistat in patients stable on propafenone hydrochloride extended-release capsules has resulted in convulsions, atrioventricular block, and circulatory failure. (7.4)
- Concomitant use of lidocaine may increase central nervous system side effects. (7.6)

FULL PRESCRIBING INFORMATION

WARNING: MORTALITY

- In the National Heart, Lung, and Blood Institute’s Cardiac Arrhythmia Suppression Trial (CAST), a long-term, multicenter, randomized, double-blind trial in patients with asymptomatic non-life-threatening ventricular arrhythmias who had a myocardial infarction more than 6 days but less than 2 years previously, an increased rate of death or reversed cardiac arrest rate (7.7%; 56/730) was seen in patients treated with encainide or flecainide (Class IC antiarrhythmics) compared with that seen in patients assigned to placebo (3 %; 22/725). The average duration of treatment with encainide or flecainide in this trial was 10 months.
- The applicability of the CAST results to other populations (e.g., those without recent myocardial infarction) or other antiarrhythmic drugs is uncertain, but at present, it is prudent to consider any IC antiarrhythmic to have a significant proarrhythmic risk in patients with structural heart disease. Given the lack of any evidence that these drugs improve survival, antiarrhythmic agents should generally be avoided in patients with non-life-threatening ventricular arrhythmias, even if the patients are experiencing unpleasant, but not life-threatening, symptoms or signs.

1 INDICATIONS AND USAGE

Propafenone hydrochloride extended-release capsules are indicated to prolong the time to recurrence of symptomatic atrial fibrillation (AF) in patients with episodic (most likely paroxysmal or persistent) AF who do not have structural heart disease.

Usage Considerations:

- The use of propafenone hydrochloride extended-release capsules in patients with permanent AF or in patients exclusively with atrial flutter or paroxysmal supraventricular tachycardia (PSVT) has not been evaluated. Do not use propafenone hydrochloride extended-release capsules to control ventricular rate during AF.
- Some patients with atrial flutter treated with propafenone have developed 1:1 conduction, producing an increase in ventricular rate. Concomitant treatment with drugs that increase the functional atrioventricular (AV) nodal refractory period is recommended.
- The effect of propafenone on mortality has not been determined [see Boxed Warning].

2 DOSAGE AND ADMINISTRATION

Propafenone hydrochloride extended-release capsules can be taken with or without food. Do not crush or further divide the contents of the capsule.

The dose of propafenone hydrochloride extended-release capsules must be individually titrated on the basis of response and tolerance. Initiate therapy with propafenone hydrochloride extended-release capsules 225 mg given every 12 hours. Dosage may be increased at a minimum of 5-day intervals to 325 mg given every 12 hours. If additional therapeutic effect is needed, the dose of propafenone hydrochloride extended-release capsules may be increased to 425 mg given every 12 hours.

In patients with hepatic impairment or those with significant widening of the QRS complex or second- or third-degree AV block, consider reducing the dose.

The combination of cytochrome P450 3A4 (CYP3A4) inhibition and either cytochrome P450 2D6 (CYP2D6) deficiency or CYP2D6 inhibition with the simultaneous administration of propafenone may significantly increase the concentration of propafenone and thereby increase the risk of proarrhythmia and other adverse events. Therefore, avoid simultaneous use of propafenone hydrochloride extended-release capsules with both a CYP2D6 inhibitor and a CYP3A4 inhibitor [see Warnings and Precautions (5.4), Drug Interactions (7.1)].

3 DOSAGE FORMS AND STRENGTHS

Propafenone Hydrochloride Extended-Release Capsules USP are supplied as hard gelatin capsules containing 225 mg, 325 mg or 425 mg of propafenone hydrochloride, USP.

The 225 mg capsule has a white opaque body imprinted with “408” in black ink and white opaque cap imprinted with Glenmark logo “G” in black ink.

The 325 mg capsule has a white opaque body imprinted with “409” in black ink and white opaque cap imprinted with Glenmark logo “G” in black ink.

The 425 mg capsule has a white opaque body imprinted with “410” and single band in black ink and white opaque cap imprinted with Glenmark logo “G” and single band in black ink.

4 CONTRAINDICATIONS

Propafenone hydrochloride extended-release capsules are contraindicated in the following circumstances:

- Heart failure
- Cardiogenic shock
- Sinoatrial, atrioventricular and intraventricular disorders of impulse generation or conduction (e.g., sick sinus node syndrome, AV block) in the absence of an artificial pacemaker
- Known Brugada Syndrome
- Bradycardia
- Marked hypotension
- Bronchospastic disorders or severe obstructive pulmonary disease
- Marked electrolyte imbalance

5 WARNINGS AND PRECAUTIONS

5.1 Proarrhythmic Effects

Propafenone has caused new or worsened arrhythmias. Such proarrhythmic effects include sudden death and life-threatening ventricular arrhythmias such as ventricular fibrillation, ventricular tachycardia, asystole and torsade de pointes. It may also worsen premature ventricular contractions or supraventricular arrhythmias, and it may prolong the QT interval. It is therefore essential that each patient given propafenone hydrochloride extended-release capsules be evaluated electrocardiographically prior to and during therapy to determine whether the response to propafenone hydrochloride extended-release capsules supports continued treatment. Because propafenone prolongs the QRS interval in the electrocardiogram, changes in the QT interval are difficult to interpret [see Clinical Pharmacology (12.2)].

In the propafenone hydrochloride extended-release capsules Atrial Fibrillation Trial (RAFT) trial [see Clinical Studies (14)], there were too few deaths to assess the long-term risk to patients. There were 5 deaths, 3 in the pooled group for propafenone hydrochloride extended-release capsules (0.8%) and 2 in the placebo group (1.6%). In the overall database of 8 trials of propafenone hydrochloride extended-release capsules and immediate-release propafenone hydrochloride, the mortality rate was 2.5% per year on propafenone and 4% per year on placebo. Concurrent use of propafenone with other antiarrhythmic agents has not been well studied.

In a U.S. uncontrolled, open-label, multicenter trial using the immediate-release formulation in patients with symptomatic supraventricular tachycardia (SVT), 1.9% (9/474) of these patients experienced ventricular tachycardia (VT) or ventricular fibrillation (VF) during the trial. However, in 4 of the 9 patients, the ventricular tachycardia was of atrial origin. Six of the 9 patients that developed ventricular arrhythmias did so within 14 days of onset of therapy. About 2.3% (11/474) of all patients had recurrence of SVT during the trial which could have been a change in the patients’ arrhythmia behavior or could represent a proarrhythmic event. Case reports in patients treated with propafenone for atrial fibrillation/flutter have included increased premature ventricular contractions (PVCs), VT, VF, torsades de pointes, asystole, and death.

Overall in clinical trials with propafenone hydrochloride immediate-release (which included patients treated for ventricular arrhythmias, atrial fibrillation/flutter, and PSVT), 4.7% of all patients had new or worsened ventricular arrhythmia possibly representing a proarrhythmic event (0.7% was an increase in PVCs; 4% a worsening or new appearance of VT or VF). Of the patients who had worsening of VT (4%), 92% had a history of VT and/or VT/VF, 71% had coronary artery disease, and 68% had a prior myocardial infarction. The incidence of proarrhythmia in patients with less serious or benign arrhythmias, which include patients with an increase in frequency of PVCs, was 1.6%. Although most proarrhythmic events occurred during the first week of therapy, late events also were seen and the CAST trial [see Boxed Warning: Mortality] suggests that an increased risk of proarythmia is present throughout treatment.

5.2 Unmasking Brugada Syndrome

Brugada Syndrome may be unmasked after exposure to propafenone hydrochloride extended-release capsules. Perform an ECG after initiation of propafenone hydrochloride extended-release capsules and discontinue the drug if changes are suggestive of Brugada Syndrome [see Contraindications (4)].

5.3 Use with Drugs that Prolong the QT Interval and Antiarrhythmic Agents

The use of propafenone hydrochloride extended-release capsules in conjunction with other drugs that prolong the QT interval has not been extensively studied. Such drugs may include many antiarrhythmics, some phenothiazines, tricyclic antidepressants, and oral macrolides. Withhold Class IA and III antiarrhythmic agents for at least 5 half-lives prior to dosing with propafenone hydrochloride extended-release capsules. Avoid the use of propafenone with Class IA and III antiarrhythmic agents (including quinidine and amiodarone). There is only limited experience with the concomitant use of Class IB or IC antiarrhythmics.

5.4 Drug Interactions: Simultaneous Use with Inhibitors of Cytochrome P450 Isoenzymes 2D6 and 3A4

Propafenone is metabolized by CYP2D6, CYP3A4, and CYP1A2 isoenzymes. Approximately 6% of Caucasians in the U.S. population are naturally deficient in CYP2D6 activity and other demographic groups are deficient to a somewhat lesser extent. Drugs that inhibit these CYP pathways (such as desipramine, paroxetine, ritonavir, sertraline for CYP2D6; ketoconazole, erythromycin, saquinavir, and grapefruit juice for CYP3A4; and amiodarone and tobacco smoke for CYP1A2) can be expected to cause increased plasma levels of propafenone.

Increased exposure to propafenone may lead to cardiac arrhythmias and exaggerated beta-adrenergic blocking activity. Because of its metabolism, the combination of CYP3A4 inhibition and either CYP2D6 deficiency or CYP2D6 inhibition in users of propafenone is potentially hazardous. Therefore, avoid simultaneous use of propafenone hydrochloride extended-release capsules with both a CYP2D6 inhibitor and a CYP3A4 inhibitor.

5.5 Use in Patients with a History of Heart Failure

Propafenone exerts a negative inotropic activity on the myocardium as well as beta-blockade effects and may provoke overt heart failure. In the U.S. trial (RAFT) in patients with symptomatic AF, heart failure was reported in 4 (1%) patients receiving propafenone hydrochloride extended-release capsules (all doses) compared with 1 (0.8%) patient receiving placebo. Proarrhythmic effects more likely occur when propafenone is administered to patients with heart failure (NYHA III and IV) or severe myocardial ischemia [see Contraindications (4)].

In clinical trial experience with propafenone hydrochloride immediate-release, new or worsened congestive heart failure has been reported in 3.7% of patients with ventricular arrhythmia. These events were more likely in subjects with pre-existing heart failure and coronary artery disease. New onset of heart failure attributable to propafenone developed in less than 0.2% of patients with ventricular arrhythmia and in 1.9% of patients with paroxysmal AF or PSVT.

5.6 Conduction Disturbances

Propafenone slows atrioventricular conduction and may also cause dose-related first-degree AV block. Average PR interval prolongation and increases in QRS duration are also dose-related. Do not give propafenone to patients with atrioventricular and intraventricular conduction defects in the absence of a pacemaker [see Contraindications (4), Clinical Pharmacology (12.2)].

In a U.S. trial (RAFT) in 523 patients with a history of symptomatic AF treated with propafenone hydrochloride extended-release capsules, sinus bradycardia (rate less than 50 beats/min) was reported with the same frequency with propafenone hydrochloride extended-release capsules and placebo.

5.7 Effects on Pacemaker Threshold

Propafenone may alter both pacing and sensing thresholds of implanted pacemakers and defibrillators. During and after therapy, monitor and re-program these devices accordingly.

5.8 Agranulocytosis

Agranulocytosis has been reported in patients receiving propafenone. Generally, the agranulocytosis occurred within the first 2 months of propafenone therapy and upon discontinuation of therapy the white count usually normalized by 14 days. Unexplained fever or decrease in white cell count, particularly during the initial 3 months of therapy, warrant consideration of possible agranulocytosis or granulocytopenia. Instruct patients to report promptly any signs of infection such as fever, sore throat, or chills.

5.9 Use in Patients with Hepatic Dysfunction

Propafenone is highly metabolized by the liver. Severe liver dysfunction increases the bioavailability of propafenone to approximately 70% compared with 3% to 40% in patients with normal liver function when given propafenone hydrochloride immediate-release tablets. In 8 patients with moderate to severe liver disease administered propafenone hydrochloride immediate-release tablets, the mean half-life was approximately 9 hours. No trials have compared bioavailability of propafenone from propafenone hydrochloride extended-release capsules in patients with normal and impaired hepatic function. Increased bioavailability of propafenone in these patients may result in excessive accumulation. Carefully monitor patients with impaired hepatic function for excessive pharmacological effects [see Overdosage (10)].

5.10 Use in Patients with Renal Dysfunction

Approximately 50% of propafenone metabolites are excreted in the urine following administration of propafenone hydrochloride immediate-release tablets. No trials have been performed to assess the percentage of metabolites eliminated in the urine following the administration of propafenone hydrochloride extended-release capsules.

In patients with impaired renal function, monitor for signs of overdosage [see Overdosage (10)].

5.11 Use in Patients with Myasthenia Gravis

Exacerbation of myasthenia gravis has been reported during propafenone therapy.

5.12 Elevated ANA Titers

Positive ANA titers have been reported in patients receiving propafenone. They have been reversible upon cessation of treatment and may disappear even in the face of continued propafenone therapy. These laboratory findings were usually not associated with clinical symptoms, but there is one published case of drug-induced lupus erythematosis (positive rechallenge); it resolved completely upon discontinuation of therapy. Carefully evaluate patients who develop an abnormal ANA test and if persistent or worsening elevation of ANA titers is detected, consider discontinuing therapy.

6 ADVERSE REACTIONS

6.1 Clinical Trials Experience

Because clinical trials are conducted under widely varying conditions, adverse reaction rates observed in the clinical trials of a drug cannot be directly compared with rates in the clinical trials of another drug and may not reflect the rates observed in practice.

The data described below reflect exposure to propafenone hydrochloride extended-release capsules 225 mg twice daily in 126 patients, to propafenone hydrochloride extended-release capsules 325 mg twice daily in 135 patients, to propafenone hydrochloride extended-release capsules 425 mg twice daily in 136 patients, and to placebo in 126 patients for up to 39 weeks (mean: 20 weeks) in a placebo-controlled trial (RAFT) conducted in the U.S. The most commonly reported adverse events with propafenone (greater than 5% and greater than placebo), excluding those not reasonably associated with the use of the drug or because they were associated with the condition being treated, were dizziness, palpitations, chest pain, dyspnea, taste disturbance, nausea, fatigue, anxiety, constipation, upper respiratory tract infection, edema, and influenza. The frequency of discontinuation due to adverse events was 17%, and the rate was highest during the first 14 days of treatment.

Cardiac-related adverse events occurring in greater than or equal to 2% of the patients in any of the RAFT propafenone extended-release treatment groups and more common with propafenone than with placebo, excluding those that are common in the population and those not plausibly related to drug therapy, included the following: angina pectoris, atrial flutter, AV block first-degree, bradycardia, congestive cardiac failure, cardiac murmur, edema, dyspnea, rales, wheezing, and cardioactive drug level above therapeutic.

Propafenone prolongs the PR and QRS intervals in patients with atrial and ventricular arrhythmias. Prolongation of the QRS interval makes it difficult to interpret the effect of propafenone on the QT interval [see Clinical Pharmacology (12.2)].

Non-cardiac related adverse events occurring in greater than or equal to 2% of the patients in any of the RAFT propafenone extended-release treatment groups and more common with propafenone than with placebo, excluding those that are common in the population and those not plausibly related to drug therapy, included the following: blurred vision, constipation, diarrhea, dry mouth, flatulence, nausea, vomiting, fatigue, weakness, upper respiratory tract infection, blood alkaline phosphatase increased, hematuria, muscle weakness, dizziness (excluding vertigo), headache, taste disturbance, tremor, somnolence, anxiety, depression, ecchymosis.

No clinically important differences in incidence of adverse reactions were noted by age or gender. Too few non-Caucasian patients were enrolled to assess adverse events according to race.

Adverse events occurring in 2% or more of the patients in any of the ERAFT [see Clinical Studies (14)] propafenone extended-release treatment groups and not listed above include the following: bundle branch block left, bundle branch block right, conduction disorders, sinus bradycardia, and hypotension.

Other adverse events reported with propafenone clinical trials not already listed elsewhere in the prescribing information include the following adverse events by body system and preferred term.

Blood and Lymphatic System

Anemia, lymphadenopathy, spleen disorder, thrombocytopenia.

Cardiac

Unstable angina, atrial hypertrophy, cardiac arrest, coronary artery disease, extrasystoles, myocardial infarction, nodal arrhythmia, palpitations, pericarditis, sinoatrial block, sinus arrest, sinus arrhythmia, supraventricular extrasystoles, ventricular extrasystoles, ventricular hypertrophy.

Ear and Labyrinth

Hearing impaired, tinnitus, vertigo.

Eye

Eye hemorrhage, eye inflammation, eyelid ptosis, miosis, retinal disorder, visual acuity reduced.

Gastrointestinal

Abdominal distension, abdominal pain, duodenitis, dyspepsia, dysphagia, eructation, gastritis, gastroesophageal reflux disease, gingival bleeding, glossitis, glossodynia, gum pain, halitosis, intestinal obstruction, melena, mouth ulceration, pancreatitis, peptic ulcer, rectal bleeding, sore throat.

General Disorders and Administration Site Conditions

Chest pain, feeling hot, hemorrhage, malaise, pain, pyrexia.

Hepatobiliary

Hepatomegaly.

Investigations

Abnormal heart sounds, abnormal pulse, carotid bruit, decreased blood chloride, decreased blood pressure, decreased blood sodium, decreased hemoglobin, decreased neutrophil count, decreased platelet count, decreased prothrombin level, decreased red blood cell count, decreased weight, glycosuria present, increased alanine aminotransferase, increased aspartate aminotransferase, increased blood bilirubin, increased blood cholesterol, increased blood creatinine, increased blood glucose, increased blood lactate dehydrogenase, increased blood pressure, increased blood prolactin, increased blood triglycerides, increased blood urea, increased blood uric acid, increased eosinophil count, increased gamma-glutamyltransferase, increased monocyte count, increased prostatic specific antigen, increased prothrombin level, increased weight, increased white blood cell count, ketonuria present, proteinuria present.

Metabolism and Nutrition

Anorexia, dehydration, diabetes mellitus, gout, hypercholesterolemia, hyperglycemia, hyperlipidemia, hypokalemia.

Musculoskeletal, Connective Tissue and Bone

Arthritis, bursitis, collagen-vascular disease, costochondritis, joint disorder, muscle cramps, muscle spasms, myalgia, neck pain, pain in jaw, sciatica, tendonitis.

Nervous System

Amnesia, ataxia, balance impaired, brain damage, cerebrovascular accident, dementia, gait abnormal, hypertonia, hypothesia, insomnia, paralysis, paresthesia, peripheral neuropathy, speech disorder, syncope, tongue hypoesthesia.

Psychiatric

Decreased libido, emotional disturbance, mental disorder, neurosis, nightmare, sleep disorder.

Renal and Urinary

Dysuria, nocturia, oliguria, pyuria, renal failure, urinary casts, urinary frequency, urinary incontinence, urinary retention, urine abnormal.

Reproductive System and Breast

Breast pain, impotence, prostatism.

Respiratory, Thoracic and Mediastinal

Atelectasis, breath sounds decreased, chronic obstructive airways disease, cough, epistaxis, hemoptysis, lung disorder, pleural effusion, pulmonary congestion, rales, respiratory failure, rhinitis, throat tightness.

Skin and Subcutaneous Tissue

Alopecia, dermatitis, dry skin, erythema, nail abnormality, petechiae, pruritus, sweating increased, urticaria.

Vascular

Arterial embolism limb, deep limb venous thrombosis, flushing, hematoma, hypertension, hypertensive crisis, hypotension, labile blood pressure, pallor, peripheral coldness, peripheral vascular disease, thrombosis.

7 DRUG INTERACTIONS

7.1 CYP2D6 and CYP3A4 Inhibitors

Drugs that inhibit CYP2D6 (such as desipramine, paroxetine, ritonavir, sertraline) and CYP3A4 (such as ketoconazole, ritonavir, saquinavir, erythromycin, and grapefruit juice) can be expected to cause increased plasma levels of propafenone. The combination of CYP3A4 inhibition and either CYP2D6 deficiency or CYP2D6 inhibition with administration of propafenone may increase the risk of adverse reactions, including proarrhythmia. Therefore, simultaneous use of propafenone hydrochloride extended-release capsules with both a CYP2D6 inhibitor and a CYP3A4 inhibitor should be avoided [see Warnings and Precautions (5.4) and Dosage and Administration (2)].

Amiodarone

Concomitant administration of propafenone and amiodarone can affect conduction and repolarization and is not recommended.

Cimetidine

Concomitant administration of propafenone immediate-release tablets and cimetidine in 12 healthy subjects resulted in a 20% increase in steady-state plasma concentrations of propafenone.

Fluoxetine

Concomitant administration of propafenone and fluoxetine in extensive metabolizers increased the S-propafenone Cmax and AUC by 39% and 50% respectively and the R-propafenone Cmax and AUC by 71% and 50%, respectively.

Quinidine

Small doses of quinidine completely inhibit the CYP2D6 hydroxylation metabolic pathway, making all patients, in effect, slow metabolizers [see Clinical Pharmacology (12.3)]. Concomitant administration of quinidine (50 mg 3 times daily) with 150 mg immediate-release propafenone 3 times daily decreased the clearance of propafenone by 60% in extensive metabolizers, making them poor metabolizers. Steady-state plasma concentrations increased by more than 2-fold for propafenone and decreased 50% for 5-OH-propafenone. A 100 mg dose of quinidine increased steady-state concentrations of propafenone 3-fold. Avoid concomitant use of propafenone and quinidine.

Rifampin

Concomitant administration of rifampin and propafenone in extensive metabolizers decreased the plasma concentrations of propafenone by 67% with a corresponding decrease of 5-OH-propafenone by 65%. The concentrations of norpropafenone increased by 30%. In poor metabolizers, there was a 50% decrease in propafenone plasma concentrations and an increase in the AUC and Cmax of norpropafenone by 74% and 20%, respectively. Urinary excretion of propafenone and its metabolites decreased significantly. Similar results were noted in elderly patients: Both the AUC and Cmax of propafenone decreased by 84%, with a corresponding decrease in AUC and Cmax of 5-OH-propafenone by 69% and 57% respectively.

7.2 Digoxin

Concomitant use of propafenone and digoxin increased steady-state serum digoxin exposure (AUC) in patients by 60% to 270% and decreased the clearance of digoxin by 31% to 67%. Monitor plasma digoxin levels of patients receiving propafenone and adjust digoxin dosage as needed.

7.3 Warfarin

The concomitant administration of propafenone and warfarin increased warfarin plasma concentrations at steady state by 39% in healthy volunteers and prolonged the prothrombin time (PT) in patients taking warfarin. Adjust the warfarin dose as needed by monitoring INR (international normalized ratio).

7.4 Orlistat

Orlistat may limit the fraction of propafenone available for absorption. In postmarketing reports, abrupt cessation of orlistat in patients stabilized on propafenone has resulted in severe adverse events including convulsions, atrioventricular block and acute circulatory failure.

7.5 Beta-Antagonists

Concomitant use of propafenone and propranolol in healthy subjects increased propranolol plasma concentrations at steady state by 113%. In 4 patients, administration of metoprolol with propafenone increased the metoprolol plasma concentrations at steady state by 100% to 400%. The pharmacokinetics of propafenone was not affected by the coadministration of either propranolol or metoprolol. In clinical trials using propafenone immediate-release tablets, patients who were receiving beta-blockers concurrently did not experience an increased incidence of side effects.

7.6 Lidocaine

No significant effects on the pharmacokinetics of propafenone or lidocaine have been seen following their concomitant use in patients. However, concomitant use of propafenone and lidocaine has been reported to increase the risks of central nervous system side effects of lidocaine.

8 USE IN SPECIFIC POPULATIONS

8.1 Pregnancy

Risk Summary

In the absence of studies in pregnant women, available data from published case reports and several decades of

postmarketing experience with use of propafenone hydrochloride extended-release capsules in pregnancy have not identified any drug-associated risks of miscarriage, birth defects, or adverse maternal or fetal outcomes. Untreated arrhythmias during pregnancy may pose a risk to the pregnant woman and fetus (see Clinical Considerations). Propafenone and its metabolite, 5-OH-propafenone, cross the placenta in humans. In animal studies, propafenone was not teratogenic. At maternally toxic doses (ranging from 2 to 6 times the maximum recommended human dose [MRHD]), there was evidence of adverse developmental outcomes when administered to pregnant rabbits and rats during organogenesis or when administered to pregnant rats during mid-gestation through weaning of their offspring (see Data).

The estimated background risks of major birth defects and miscarriage for the indicated populations are unknown. All pregnancies have a background risk of birth defect, loss, or other adverse outcomes. In the U.S. general population, the estimated background risk of major birth defects and miscarriage in clinically recognized pregnancies is 2% to 4% and 15% to 20%, respectively.

Clinical Considerations

Disease-associated maternal and/or embryo/fetal risk: The incidence of VT is increased and may be more symptomatic during pregnancy. Ventricular arrhythmias most often occur in pregnant women with underlying cardiomyopathy, congenital heart disease, valvular heart disease, or mitral valve prolapse. Breakthrough arrhythmias may also occur during pregnancy, as therapeutic treatment levels may be difficult to maintain due to the increased volume of distribution and increased drug metabolism inherent in the pregnant state.

Fetal/Neonatal Adverse Reactions: Propafenone and its metabolite have been shown to cross the placenta. Adverse reactions such as fetal/neonatal arrhythmias have been associated with the use of other antiarrhythmic agents by pregnant women. Fetal/neonatal monitoring for signs and symptoms of arrhythmia is recommended during and after treatment of pregnant women with propafenone.

Labor or Delivery: Risk of arrhythmias may increase during labor and delivery. Patients treated with propafenone hydrochloride extended-release capsules should be monitored continuously for arrhythmias during labor and delivery [see Warnings and Precautions (5.1)].

Data

Propafenone has been shown to cause embryo-fetal mortality in rabbits and rats when given orally during organogenesis at maternally toxic doses of 150 mg/kg/day (rabbit: maternal mortality, decreased body weight gain and food consumption at approximately 3 times the MRHD on a mg/m^2 basis) and 600 mg/kg/day (rat: maternal decreased body weight gain and food consumption at approximately 6 times the MRHD on a mg/m^2 basis). In addition, a maternally toxic dose of 600 mg/kg/day (approximately 6 times the MRHD on a mg/m^2 basis) also caused decreased fetal weights in rats. Increased placental weights and delayed ossification occurred in rabbits at a dose of 30 mg/kg/day (less than the MRHD on a mg/m^2 basis) in the absence of maternal toxicity. No adverse developmental outcomes in the absence of maternal toxicity were seen following oral doses of 15 mg/kg/day to rabbits or up to 270 mg/kg/day to rats administered during organogenesis (equivalent to 0.3 times or approximately 3 times the MRHD on a mg/m^2 basis, respectively). In an oral study, female rats received propafenone up to 500 mg/kg/day from mid-gestation through weaning. At 90 mg/kg/day (equivalent to the MRHD on a mg/m^2 basis), there were no adverse developmental outcomes in the absence of maternal toxicity. However, doses ≥180 mg/kg/day (2 or more times the MRHD on a mg/m^2 basis) produced increases in maternal deaths and resulted in reductions in neonatal survival, body weight gain, and delayed development in the presence of maternal toxicity.

8.2 Lactation

Risk Summary

Propafenone and its active metabolite, 5-OH-propafenone, are present in human milk, but the levels are likely to be low.

There are no data on the effects of propafenone on the breastfed infant or the effects on milk production.

The developmental and health benefits of breastfeeding should be considered along with the mother’s clinical need for

propafenone and any potential adverse effects on the breastfed infant from propafenone or from the underlying maternal

condition.

8.3 Females and Males of Reproductive Potential

Infertility

Males: Based on human and animal studies, propafenone hydrochloride extended-release capsules may transiently impair spermatogenesis in males. Evaluation of the effects on spermatogenesis was performed in 11 healthy males given oral propafenone 300 mg b.i.d. for 4 days, which was then increased to 300 mg t.i.d. for an additional 4 days. Study findings included a 28% reduction in semen sample volume on Treatment Day 8 and a 27% reduction in sperm count 64 days after treatment (both values remained within the laboratories normal reference range). These effects were not seen in follow-up visits up to 120 days after treatment. Reversible decreases in spermatogenesis have been demonstrated in monkeys, dogs, and rabbits after lethal or near-lethal intravenous doses of propafenone [see Nonclinical Toxicology (13.1)].

8.4 Pediatric Use

The safety and effectiveness of propafenone in pediatric patients have not been established.

8.5 Geriatric Use

Of the total number of subjects in Phase 3 clinical trials of propafenone hydrochloride extended-release 46% were 65 and older, while 16% were 75 and older. No overall differences in safety or effectiveness were observed between these subjects and younger subjects, but greater sensitivity of some older individuals at higher doses cannot be ruled out. The effect of age on the pharmacokinetics and pharmacodynamics of propafenone has not been studied.

10 OVERDOSAGE

The symptoms of overdosage may include hypotension, somnolence, bradycardia, intra-atrial and intraventricular conduction disturbances, and rarely convulsions and high-grade ventricular arrhythmias. Defibrillation as well as infusion of dopamine and isoproterenol has been effective in controlling abnormal rhythm and blood pressure. Convulsions have been alleviated with intravenous diazepam. General supportive measures such as mechanical respiratory assistance and external cardiac massage may be necessary.

The hemodialysis of propafenone in patients with an overdose is expected to be of limited value in the removal of propafenone as a result of both its high protein binding (greater than 95%) and large volume of distribution.

11 DESCRIPTION

Propafenone Hydrochloride Extended-Release Capsules USP are an antiarrhythmic drug supplied in extended-release capsules of 225 mg, 325 mg and 425 mg for oral administration.

Chemically, propafenone hydrochloride, USP is 2’-[2-hydroxy-3-(propylamino)-propoxy]-3-phenylpropiophenone hydrochloride, with a molecular weight of 377.9 g/mol. The molecular formula is C21H27NO3•HCl.

Propafenone hydrochloride, USP has some structural similarities to beta-blocking agents. The structural formula of propafenone hydrochloride, USP is given below:

Propafenone hydrochloride, USP occurs as a white to almost white powder or crystals. It is soluble in methanol and in hot water; slightly soluble in alcohol and in chloroform; very slightly soluble in acetone; insoluble in diethyl ether and in toluene.

Propafenone Hydrochloride Extended-Release Capsules USP are filled with white to off white colored, round shaped flat mini tablets, containing propafenone hydrochloride, USP and the following inactive ingredients: black iron oxide, gelatin, hypromellose, lactose monohydrate, magnesium stearate, microcrystalline cellulose, potassium hydroxide, shellac, sodium lauryl sulfate and titanium dioxide.

USP dissolution test is pending.

12 CLINICAL PHARMACOLOGY

12.1 Mechanism of Action

Propafenone is a Class 1C antiarrhythmic drug with local anesthetic effects and a direct stabilizing action on myocardial membranes. The electrophysiological effect of propafenone manifests itself in a reduction of upstroke velocity (Phase 0) of the monophasic action potential. In Purkinje fibers, and to a lesser extent myocardial fibers, propafenone reduces the fast inward current carried by sodium ions. Diastolic excitability threshold is increased and effective refractory period prolonged. Propafenone reduces spontaneous automaticity and depresses triggered activity.

Studies in anesthetized dogs and isolated organ preparations show that propafenone has beta-sympatholytic activity at about 1/50 the potency of propranolol. Clinical studies employing isoproterenol challenge and exercise testing after single doses of propafenone indicate a beta-adrenergic blocking potency (per mg) about 1/40 that of propranolol in man. In clinical trials with the immediate-release formulation, resting heart rate decreases of about 8% were noted at the higher end of the therapeutic plasma concentration range. At very high concentrations in vitro, propafenone can inhibit the slow inward current carried by calcium, but this calcium antagonist effect probably does not contribute to antiarrhythmic efficacy. Moreover, propafenone inhibits a variety of cardiac potassium currents in in vitro studies (i.e., the transient outward, the delayed rectifier, and the inward rectifier current). Propafenone has local anesthetic activity approximately equal to procaine. Compared with propafenone, the main metabolite, 5-hydroxypropafenone, has similar sodium and calcium channel activity, but about 10 times less beta-blocking activity (N-depropylpropafenone has weaker sodium channel activity but equivalent affinity for beta-receptors).

12.2 Pharmacodynamics

Cardiac Electrophysiology

Electrophysiology trials in patients with ventricular tachycardia have shown that propafenone prolongs atrioventricular conduction while having little or no effect on sinus node function. Both atrioventricular nodal conduction time (AH interval) and His-Purkinje conduction time (HV interval) are prolonged. Propafenone has little or no effect on the atrial functional refractory period, but AV nodal functional and effective refractory periods are prolonged. In patients with Wolff-Parkinson-White syndrome, propafenone hydrochloride immediate-release tablets reduce conduction and increase the effective refractory period of the accessory pathway in both directions.

Electrocardiograms: Propafenone prolongs the PR and QRS intervals. Prolongation of the QRS interval makes it difficult to interpret the effect of propafenone on the QT interval.

Table 1. Mean Change ± SD in 12-Lead Electrocardiogram Results (RAFT)
 | Propafenone Hydrochloride Extended-Release Capsules Twice-Daily Dosing |  |  | Placebo
 | 225 mg | 325 mg | 425 mg | Placebo
 | N=126 | N=135 | N=136 | N=126
PR (ms) | 9±22 | 12±23 | 21±24 | 1±16
QRS (ms) | 4±14 | 6±15 | 6±15 | -2±12
Heart rate | 5±24 | 7±23 | 2±22 | 8±27
QTca (ms) | 2±30 | 5±36 | 6±37 | 5±35

aCalculated using Bazett’s correction factor

In RAFT [see Clinical Studies (14)], the distribution of the maximum changes in QTc compared with baseline over the trial in each patient was similar in the groups receiving propafenone hydrochloride extended-release capsules 225 mg twice daily, 325 mg twice daily, and 425 mg twice daily and placebo. Similar results were seen in the ERAFT trial.

Table 2. Number of Patients According to the Range of Maximum QTc change compared with baseline over the Trial in each dose group (RAFT Trial).
Range maximum QTc change | Propafenone Hydrochloride Extended-release Capsules |  |  | Placebo
 | 225 mg Twice Daily | 325 mg Twice Daily | 425 mg Twice Daily
 | N=119 | N=129 | N=123 | N=100
 | n (%) | n (%) | n (%) | n (%)
>20% | 1 (1) | 6 (5) | 3 (2) | 5 (4)
10 to 20% | 19 (16) | 28 (22) | 32 (26) | 24 (20)
0≤10% | 99 (83) | 95 (74) | 88 (72) | 91 (76)

Hemodynamics Trials in humans have shown that propafenone exerts a negative inotropic effect on the myocardium. Cardiac catheterization trials in patients with moderately impaired ventricular function (mean CI: 2.61 L/min/m^2), utilizing intravenous propafenone infusions (loading dose of 2 mg/kg over 10 min+ followed by 2 mg/min for 30 min) that gave mean plasma concentrations of 3 mcg/mL (a dose that produces plasma levels of propafenone greater than recommended oral dosing), showed significant increases in pulmonary capillary wedge pressure, systemic and pulmonary vascular resistances and depression of cardiac output and cardiac index.

12.3 Pharmacokinetics

Absorption/Bioavailability

Maximal plasma levels of propafenone are reached between 3 to 8 hours following the administration of propafenone hydrochloride extended-release capsules. Propafenone is known to undergo extensive and saturable presystemic biotransformation which results in a dose-dependent and dosage-form-dependent absolute bioavailability; e.g., a 150 mg immediate-release tablet had an absolute bioavailability of 3.4%, while a 300 mg immediate-release tablet had an absolute bioavailability of 10.6%. Absorption from a 300 mg solution dose was rapid, with an absolute bioavailability of 21.4%. At still larger doses, above those recommended, bioavailability of propafenone from immediate-release tablets increased still further.

Relative bioavailability assessments have been performed between propafenone hydrochloride extended-release capsules and propafenone hydrochloride immediate-release tablets. In extensive metabolizers, the bioavailability of propafenone from the SR formulation was less than that of the immediate-release formulation as the more gradual release of propafenone from the prolonged-release preparations resulted in an increase of overall first-pass metabolism [see Metabolism]. As a result of the increased first-pass effect, higher daily doses of propafenone were required from the extended-release formulation relative to the immediate-release formulation to obtain similar exposure to propafenone. The relative bioavailability of propafenone from the 325 mg twice daily regimens of propafenone hydrochloride extended-release capsules approximates that of propafenone hydrochloride immediate-release 150 mg 3 times daily regimen. Mean exposure to 5-hydroxypropafenone was about 20% to 25% higher after extended-release capsule administration than after immediate-release tablet administration.

Food increased the exposure to propafenone 4-fold after single-dose administration of 425 mg of propafenone hydrochloride extended-release capsules. However, in the multiple dose trial (425 mg dose twice daily), the difference between the fed and fasted state was not significant.

Distribution

Following intravenous administration of propafenone, plasma levels decline in a bi-phasic manner consistent with a 2-compartment pharmacokinetic model. The average distribution half-life corresponding to the first phase was about 5 minutes. The volume of the central compartment was about 88 liters (1.1 L/kg) and the total volume of distribution about 252 liters.

In serum, propafenone is greater than 95% bound to proteins within the concentration range of 0.5 to 2 mcg/mL.

Metabolism

There are two genetically determined patterns of propafenone metabolism. In over 90% of patients, the drug is rapidly and extensively metabolized with an elimination half-life from 2 to 10 hours. These patients metabolize propafenone into two active metabolites: 5-hydroxypropafenone which is formed by CYP2D6 and N-depropylpropafenone (norpropafenone) which is formed by both CYP3A4 and CYP1A2. In less than 10% of patients, metabolism of propafenone is slower because the 5-hydroxy metabolite is not formed or is minimally formed. In these patients, the estimated propafenone elimination half-life ranges from 10 to 32 hours. Decreased ability to form the 5-hydroxy metabolite of propafenone is associated with a diminished ability to metabolize debrisoquine and a variety of other drugs such as encainide, metoprolol, and dextromethorphan whose metabolism is mediated by the CYP2D6 isozyme. In these patients, the N-depropylpropafenone metabolite occurs in quantities comparable to the levels occurring in extensive metabolizers.

As a consequence of the observed differences in metabolism, administration of propafenone hydrochloride extended-release capsules to slow and extensive metabolizers results in significant differences in plasma concentrations of propafenone, with slow metabolizers achieving concentrations about twice those of the extensive metabolizers at daily doses of 850 mg/day. At low doses the differences are greater, with slow metabolizers attaining concentrations about 3 to 4 times higher than extensive metabolizers. In extensive metabolizers, saturation of the hydroxylation pathway (CYP2D6) results in greater-than-linear increases in plasma levels following administration of propafenone hydrochloride extended-release capsules. In slow metabolizers, propafenone pharmacokinetics is linear. Because the difference decreases at high doses and is mitigated by the lack of the active 5-hydroxymetabolite in the slow metabolizers, and because steady-state conditions are achieved after 4 to 5-days of dosing in all patients, the recommended dosing regimen of propafenone hydrochloride extended-release capsules is the same for all patients. The larger inter-subject variability in blood levels requires that the dose of the drug be titrated carefully in patients with close attention paid to clinical and ECG evidence of toxicity [see Dosage and Administration (2)].

The 5-hydroxypropafenone and norpropafenone metabolites have electrophysiologic properties similar to propafenone in vitro. In man after administration of propafenone hydrochloride extended-release capsules, the 5-hydroxypropafenone metabolite is usually present in concentrations less than 40% of propafenone. The norpropafenone metabolite is usually present in concentrations less than 10% of propafenone.

Inter-Subject Variability: With propafenone, there is a considerable degree of inter-subject variability in pharmacokinetics which is due in large part to the first-pass hepatic effect and non-linear pharmacokinetics in extensive metabolizers. A higher degree of inter-subject variability in pharmacokinetic parameters of propafenone was observed following both single- and multiple-dose administration of propafenone hydrochloride extended-release capsules. Inter-subject variability appears to be substantially less in the poor-metabolizer group than in the extensive-metabolizer group, suggesting that a large portion of the variability is intrinsic to CYP2D6 polymorphism rather than to the formulation.

Stereochemistry: Propafenone hydrochloride is a racemic mixture. The R- and S-enantiomers of propafenone display stereoselective disposition characteristics. In vitro and in vivo studies have shown that the R-isomer of propafenone is cleared faster than the S-isomer via the 5-hydroxylation pathway (CYP2D6). This results in a higher ratio of S-propafenone to R-propafenone at steady state. Both enantiomers have equivalent potency to block sodium channels; however, the S-enantiomer is a more potent beta-antagonist than the R-enantiomer. Following administration of propafenone hydrochloride immediate-release tablets or propafenone hydrochloride extended-release capsules, the S/R ratio for the area under the plasma concentration-time curve was about 1.7. The S/R ratios of propafenone obtained after administration of 225 mg, 325 mg and 425 mg propafenone hydrochloride extended-release capsules are independent of dose. In addition, no difference in the average values of the S/R ratios is evident between genotypes or over time.

Specific Populations

Patients with Hepatic Impairment: Decreased liver function increases the bioavailability of propafenone. Absolute bioavailability assessments have not been determined for the propafenone hydrochloride extended-release capsule formulation. Absolute bioavailability of propafenone hydrochloride immediate-release tablets is inversely related to indocyanine green clearance, reaching 60% to 70% at clearances of 7 mL/min and below. Protein binding decreases to about 88% in patients with severe hepatic dysfunction. The clearance of propafenone is reduced and the elimination half-life increased in patients with significant hepatic dysfunction [see Warnings and Precautions (5.9)].

13 NONCLINICAL TOXICOLOGY

13.1 Carcinogenesis, Mutagenesis, Impairment of Fertility

Lifetime maximally tolerated oral dose studies in mice (up to 360 mg/kg/day, approximately twice the MRHD on a mg/m^2 basis) and rats (up to 270 mg/kg/day, approximately 3 times the MRHD on a mg/m^2 basis) provided no evidence of a carcinogenic potential for propafenone.

Propafenone was not mutagenic in the Ames (salmonella) test and the in vivo mouse dominant lethal test. Propafenone was not clastogenic in the human lymphocyte chromosome aberration assay in vitro, the rat and Chinese hamster micronucleus tests, and other in vivo tests for chromosomal aberrations in rat bone marrow and Chinese hamster bone marrow and spermatogonia.

Propafenone, administered intravenously, has been shown to decrease spermatogenesis at lethal doses in rabbits (≥3.5 mg/kg/day) or at near-lethal dose levels in monkeys and dogs (≤5 mg/kg/day); doses were less than the MRHD on a mg/m^2 basis. These effects were reversible and did not impair fertility in rabbits at an intravenous dose of 3.5 mg/kg/day (a spermatogenesis-impairing dose). Effects on spermatogenesis were not found when propafenone was administered to rats either orally or intravenously up to 360 mg/kg/day or 6 mg/kg/day, respectively, or in dogs at oral doses up to 240 mg/kg/day (up to approximately 4 or 9 times the MRHD on a mg/m^2 basis in rats and dogs, respectively). Treatment of male rabbits for 10 weeks prior to mating at an oral dose of 120 mg/kg/day (approximately 2 times the MRHD on a mg/m^2 basis) did not result in evidence of impaired fertility. Nor was there evidence of impaired fertility when propafenone was administered orally to male and female rats at dose levels up to 270 mg/kg/day (approximately 3 times the MRHD on a mg/m^2 basis) for 10 weeks (males) or 2 weeks (females) prior to mating through mating.

13.2 Animal Toxicology and/or Pharmacology

Renal changes have been observed in the rat following 6 months of oral administration of propafenone HCl at doses of 180 and 360 mg/kg/day (about 2 and 4 times, respectively, the MRHD on a mg/m^2 basis). Both inflammatory and non-inflammatory changes in the renal tubules, with accompanying interstitial nephritis, were observed. These changes were reversible, as they were not found in rats allowed to recover for 6 weeks. Fatty degenerative changes of the liver were found in rats following longer durations of administration of propafenone HCl at a dose of 270 mg/kg/day (about 3 times the MRHD on a mg/m^2 basis). There were no renal or hepatic changes at 90 mg/kg/day equivalent to the MRHD on a mg/m^2 basis).

14 CLINICAL STUDIES

Propafenone hydrochloride extended-release capsules have been evaluated in patients with a history of electrocardiographically documented recurrent episodes of symptomatic AF in 2 randomized, double-blind, placebo-controlled trials.

RAFT

In one US multicenter trial (RAFT), 3 doses of propafenone hydrochloride extended-release capsules (225 mg twice daily, 325 mg twice daily and 425 mg twice daily) and placebo were compared in 523 patients with symptomatic, episodic AF. The patient population in this trial was 59% male with a mean age of 63 years; 91% white and 6% black. The patients had a median history of AF of 13 months, and documented symptomatic AF within 12 months of trial entry. Over 90% were NYHA Class I, and 21% had a prior electrical cardioversion. At baseline, 24% were treated with calcium channel blockers, 37% with beta-blockers, and 38% with digoxin. Symptomatic arrhythmias after randomization were documented by transtelephonic electrocardiogram and centrally read and adjudicated by a blinded adverse event committee. Propafenone hydrochloride extended-release capsules administered for up to 39 weeks was shown to prolong significantly the time to the first recurrence of symptomatic atrial arrhythmia, predominantly AF, from Day 1 of randomization (primary efficacy variable) compared with placebo, as shown in Table 3.

Table 3: Analysis of Tachycardia-Free Period (Days) from Day 1 of Randomization
 | Dose of Propafenone Hydrochloride Extended-Release Capsules Twice-Daily Dose
Parameter | 225 mg; Twice Daily; (N = 126); n (%) | 325 mg; Twice Daily; (N = 135); n (%) | 425 mg; Twice Daily (N = 136) n (%) | Placebo; (N = 126) n (%)
Patients completing with terminating eventa | 66 (52) | 56 (41) | 41 (30) | 87 (69)
Comparison of tachycardia-free periods
Kaplan-Meier Media | 112 | 291 | NAb | 41
Range | 0 to 285 | 0 to 293 | 0 to 300 | 0 to 289
p-Value (Log-rank test) | 0.014 | <0.0001 | <0.0001 | --
Hazard Ratio compared with placebo | 0.67 | 0.43 | 0.35 | --
95% CI for Hazard Ratio | (0.49, 0.93) | (0.31, 0.61) | (0.24, 0.51) | --

a Terminating events comprised 91% AF, 5% atrial flutter, and 4% PSVT.
b Not Applicable: Fewer than 50% of the patients had events. The median time is not calculable.

There was a dose response for propafenone hydrochloride extended-release capsules for the tachycardia-free period as shown in the proportional hazard analysis and the Kaplan-Meier curves presented in Figure 1.

Figure 1: RAFT Kaplan-Meier Analysis for the Tachycardia-Free Period From Day 1 of Randomization

In additional analyses, propafenone hydrochloride extended-release capsules (225 mg twice daily, 325 mg twice daily, and 425 mg twice daily) were also shown to prolong time to the first recurrence of symptomatic AF from Day 5 (steady-state pharmacokinetics were attained). The antiarrhythmic effect of propafenone hydrochloride extended-release capsules was not influenced by age, gender, history of cardioversion, duration of AF, frequency of AF or use of medication that lowers heart rate. Similarly, the antiarrhythmic effect of propafenone hydrochloride extended-release capsules was not influenced by the individual use of calcium channel blockers, beta-blockers or digoxin. Too few non-white patients were enrolled to assess the influence of race on effects of propafenone hydrochloride extended-release.

No difference in the average heart rate during the first recurrence of symptomatic arrhythmia between propafenone hydrochloride extended-release capsules and placebo was observed.

ERAFT

In a European multicenter trial (European Rythmonorm SR Atrial Fibrillation Trial [ERAFT]), 2 doses of propafenone hydrochloride extended-release capsules (325 mg twice daily and 425 mg twice daily) and placebo were compared in 293 patients with documented electrocardiographic evidence of symptomatic paroxysmal AF. The patient population in this trial was 61% male, 100% white with a mean age of 61 years. Patients had a median duration of AF of 3.3 years, and 61% were taking medications that lowered heart rate. At baseline, 15% of the patients were treated with calcium channel blockers (verapamil and diltiazem), 42% with beta-blockers and 8% with digoxin. During a qualifying period of up to 28 days, patients had to have 1 ECG-documented incident of symptomatic AF. The double-blind treatment phase consisted of a 4-day loading period followed by a 91-day efficacy period. Symptomatic arrhythmias were documented by electrocardiogram monitoring.

In ERAFT, propafenone hydrochloride extended-release capsules were shown to prolong the time to the first recurrence of symptomatic atrial arrhythmia from Day 5 of randomization (primary efficacy analysis). The proportional hazard analysis revealed that both propafenone hydrochloride extended-release capsules doses were superior to placebo. The antiarrhythmic effect of propafenone extended-release was not influenced by age, gender, duration of AF, frequency of AF or use of medication that lowers heart rate. It was also not influenced by the individual use of calcium channel blockers, beta-blockers or digoxin. Too few non-white patients were enrolled to assess the influence of race on the effects of propafenone hydrochloride extended-release capsules. There was a slight increase in the incidence of centrally diagnosed asymptomatic AF or atrial flutter in each of the 2 propafenone hydrochloride extended-release treatment groups compared with placebo.

16 HOW SUPPLIED/STORAGE AND HANDLING

Propafenone Hydrochloride Extended-Release Capsules USP are supplied as hard gelatin capsules containing either 225 mg, 325 mg or 425 mg of propafenone hydrochloride, USP.

The 225 mg capsule has a white opaque body imprinted with “408” in black ink and white opaque cap imprinted with Glenmark logo “G” in black ink. They are available as follows:

NDC 68462-408-60 Bottles of 60 capsules

The 325 mg capsule has a white opaque body imprinted with “409” in black ink and white opaque cap imprinted with Glenmark logo “G” in black ink. They are available as follows:

NDC 68462-409-60 Bottles of 60 capsules

The 425 mg capsule has a white opaque body imprinted with “410” and single band in black ink and white opaque cap imprinted with Glenmark logo “G” and single band in black ink. They are available as follows:

NDC 68462-410-60 Bottles of 60 capsules

Storage: Store at 20°C to 25°C (68°F to 77°F); excursions permitted to 15°C to 30°C (59°F to 86°F) [see USP Controlled Room Temperature]. Dispense in a tight container as defined in the USP.

17 PATIENT COUNSELING INFORMATION

Advise the patient to read the FDA-approved patient labeling (Patient Information).

- Instruct patients to notify their healthcare providers of any change in over-the-counter, prescription, and supplement use.
- Instruct patients to report symptoms that may be associated with altered electrolyte balance, such as excessive or prolonged diarrhea, sweating, vomiting, or loss of appetite or thirst.
- Instruct patients not to double the next dose if a dose is missed. The next dose should be taken at the usual time.

Distributed by:

Glenmark Pharmaceuticals Inc., USA

Elmwood Park, NJ 07407

Questions? 1 (888) 721-7115

www.glenmarkpharma-us.com

August 2025

PATIENT INFORMATION

Propafenone Hydrochloride (proeʺ pa feeʹ none hye′′ droe klor′ ide)

Extended-Release Capsules

What are propafenone hydrochloride extended-release capsules?

Propafenone hydrochloride extended-release capsules are a prescription medicine that is used:

- in certain people who have a heart rhythm disorder called atrial fibrillation (AF)
- to increase the amount of time between having symptoms of AF

It is not known if propafenone hydrochloride extended-release capsules are safe and effective in children.

Who should not take propafenone hydrochloride extended-release capsules?

Do not take propafenone hydrochloride extended-release capsules if you have:

- heart failure (weak heart)
- had a recent heart attack
- a heart condition called Brugada Syndrome
- a heart rate that is too slow, and you do not have a pacemaker
- very low blood pressure
- certain breathing problems that make you short of breath or wheeze
- certain abnormal body salt (electrolyte) levels in your blood

Talk to your doctor before taking propafenone hydrochloride extended-release capsules if you think you have any of the conditions listed above.

What should I tell my doctor before taking propafenone hydrochloride extended-release capsules?

Before you take propafenone hydrochloride extended-release capsules tell your doctor if you:

- have liver or kidney problems
- have breathing problems
- have symptoms including diarrhea, sweating, vomiting, or loss of appetite or thirst that are severe. These symptoms may be a sign of abnormal electrolyte levels in your blood.
- have myasthenia gravis
- have lupus erythematosus
- have been told you have or had an abnormal blood test called Antinuclear Antibody Test or ANA Test
- are pregnant or plan to become pregnant.
- are breastfeeding or plan to breastfeed. Propafenone hydrochloride can pass into your milk. You and your doctor
should discuss the best way to feed your baby during this time.
- have any other medical conditions

Tell your doctor about all the medicines you take, including prescription and over-the-counter medicines, vitamins, and herbal supplements. Propafenone hydrochloride extended-release capsules and certain other medicines can affect each other and cause serious side effects. Propafenone hydrochloride extended-release capsules may affect the way other medicines work, and other medicines may affect how propafenone hydrochloride extended-release capsules work.

Especially tell your doctor if you take:

- amiodarone or other medicines for your abnormal heart beats
- an antidepressant medicine
- a medicine to treat anxiety
- ritonavir (for example, KALETRA, NORVIR) or saquinavir (for example, INVIRASE)
- an antibiotic medicine
- ketoconazole (for example, NIZORAL)
- digoxin (LANOXIN)
- warfarin sodium (for example, COUMADIN, JANTOVEN)

Know the medicines you take. Keep a list of them to show your doctor and pharmacist when you get a new medicine.

How should I take propafenone hydrochloride extended-release capsules?

- Take propafenone hydrochloride extended-release capsules exactly as prescribed. Your doctor will tell you how many capsules to take and how often to take them.
- To help reduce the chance of certain side effects, your doctor may start you with a low dose of propafenone hydrochloride extended-release capsules and then slowly increase the dose.
- Do not open or crush the capsule.
- You may take propafenone hydrochloride extended-release capsules with or without food.
- You should not drink grapefruit juice during treatment with propafenone hydrochloride extended-release capsules
- If you miss a dose of propafenone hydrochloride extended-release capsules take your next dose at the usual time. Do not take 2 doses at the same time.
- If you take too much propafenone hydrochloride extended-release capsules call your doctor or go to the nearest hospital emergency room right away.
- Call your doctor if your heart problems get worse.

What are possible side effects of propafenone hydrochloride extended-release capsules?
Propafenone hydrochloride extended-release capsules can cause serious side effects including:

- New or worsened abnormal heart beats, that can cause sudden death or be life-threatening. Your doctor may do an electrocardiogram (ECG or EKG) before and during treatment to check your heart for these problems.
- New or worsened heart failure. Tell your doctor about any changes in your heart symptoms, including:
  - any new or increased swelling in your arms or legs
  - trouble breathing
  - sudden weight gain
- Effects on pacemaker function. Propafenone hydrochloride extended-release capsules may affect how an implanted pacemaker or defibrillator works. Your doctor should check how your pacemaker or defibrillator is working during and after treatment with propafenone hydrochloride extended-release capsules. They may need to be re-programmed.
- Very low white blood cell levels in your blood (agranulocytosis). Your bone marrow may not produce enough of a certain type of white blood cells called neutrophils. If this happens, you are more likely to get infections. Tell your doctor right away if you have any of these symptoms, especially during the first 3 months of treatment:
  - fever
  - sore throat
  - chills
- Worsening of myasthenia gravis in people who already have this condition. Tell your doctor about any change in your symptoms.
- Propafenone hydrochloride extended-release capsules may cause lower sperm counts in men. This could affect the ability to father a child. Talk to your doctor if this is a concern for you.

Common side effects of propafenone hydrochloride extended-release capsules include:

- dizziness
- fast or irregular heart beats
- chest pain
- trouble breathing
- taste changes
- nausea
- tiredness
- feeling anxious
- constipation
- upper respiratory infection or flu
- swelling

Tell your doctor if you have any side effect that bothers you or that does not go away.
These are not all the possible side effects of propafenone hydrochloride extended-release capsules. For more information, ask your doctor or pharmacist.
Call your doctor for medical advice about side effects. You may report side effects to FDA at 1-800-FDA-1088.

How should I store propafenone hydrochloride extended-release capsules?

- Store propafenone hydrochloride extended-release capsules at room temperature between 68°F to 77°F (20°C to 25°C).
- Keep the bottle tightly closed.

Keep propafenone hydrochloride extended-release capsules and all medicines out of the reach of children.

General information about propafenone hydrochloride extended-release capsules
Medicines are sometimes prescribed for conditions other than those described in patient information leaflets. Do not use propafenone hydrochloride extended-release capsules for a condition for which it was not prescribed by your doctor. Do not give propafenone hydrochloride extended-release capsules to other people, even if they have the same symptoms you have. It may harm them.

This leaflet summarizes the most important information about propafenone hydrochloride extended-release capsules. If you would like more information, talk with your doctor. You can ask your doctor or pharmacist for information about propafenone hydrochloride extended-release capsules that is written for healthcare professionals. For more information about propafenone hydrochloride extended-release capsules call 1 (888) 721-7115.

What are the ingredients in propafenone hydrochloride extended-release capsules?
Active Ingredient: Propafenone hydrochloride

Inactive Ingredients: black iron oxide, gelatin, hypromellose, lactose monohydrate, magnesium stearate, microcrystalline cellulose, potassium hydroxide, shellac, sodium lauryl sulfate and titanium dioxide.

Brands listed are trademarks of their respective owners and are not trademarks of Glenmark Pharmaceuticals Inc., USA. The makers of these brands are not affiliated with and do not endorse Glenmark Pharmaceuticals Inc., USA or its products.

Distributed by:

Glenmark Pharmaceuticals Inc., USA

Elmwood Park, NJ 07407

Questions? 1 (888) 721-7115

www.glenmarkpharma-us.com

August 2025

Label Display Panel

NDC 68462-408-60

Propafenone Hydrochloride Extended-release Capsules

225 mg, Bottle of 60 Capsules

Package/Label Display Panel

NDC 68462-409-60

Propafenone Hydrochloride Extended-release Capsules

325 mg, Bottle of 60 Capsules

Package/Label Display Panel

NDC 68462-410-60

Propafenone Hydrochloride Extended-release Capsules

425 mg, Bottle of 60 Capsules